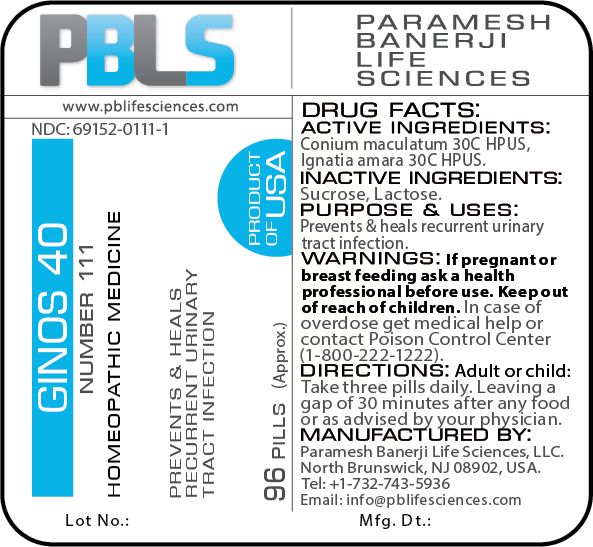 DRUG LABEL: Ginos 40 (Number 111)
NDC: 69152-0111 | Form: PELLET
Manufacturer: Paramesh Banerji Life Sciences LLC
Category: homeopathic | Type: HUMAN OTC DRUG LABEL
Date: 20180625

ACTIVE INGREDIENTS: CONIUM MACULATUM FLOWERING TOP 30 [hp_C]/1 1; STRYCHNOS IGNATII SEED 30 [hp_C]/1 1
INACTIVE INGREDIENTS: SUCROSE; LACTOSE

DRUG FACTS: Active Ingredients

Conium maculatum 30C HPUS, Ignatia amara 30C HPUS

Inactive Ingredients

Sucrose, Lactose

Purpose

Prevents & heals recurrent urinary tract infection

Uses

Prevents & heals recurrent urinary tract infection

Warnings

If pregnant or breast feeding ask a health professional before use.

Keep out of reach of children. In case of overdose, get medical help or contact a Poison Control Center (1-800-222-1222) right away.

Direction

Adult or child: Take three pills daily. Leaving a gap of 30 minutes after any food or as advised by your physician.

Manufactured by

Paramesh Banerji Life Sciences, LLC

North Brunswick, NJ 08902, USA

Tel: +1-732-743-5936

Email: info@pblifesciences.com

Principal Display Panel

NDC: 69152-0111-1

Ginos 40

Number 111

Homeopathic Medicine

Prevents & heals recurrent urinary tract infection

96 Pills (Approx.)

Product of USA